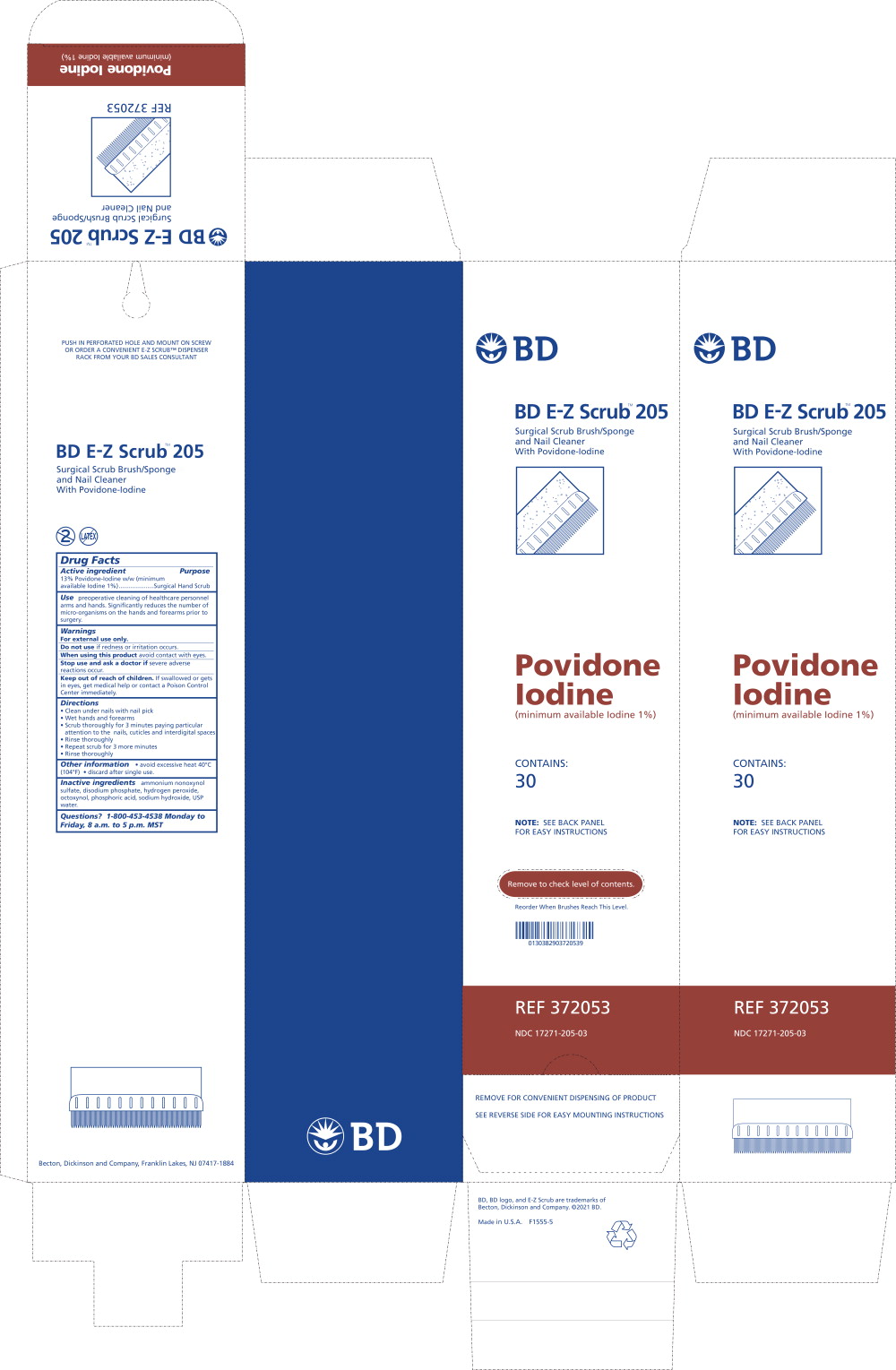 DRUG LABEL: BD E-Z SCRUB
NDC: 17271-205 | Form: SOLUTION
Manufacturer: Becton Dickinson and Company
Category: otc | Type: HUMAN OTC DRUG LABEL
Date: 20251208

ACTIVE INGREDIENTS: POVIDONE-IODINE
 100 mg/1 mL
INACTIVE INGREDIENTS: AMMONIUM NONOXYNOL-4 SULFATE; SODIUM PHOSPHATE, DIBASIC, MONOHYDRATE; HYDROGEN PEROXIDE; OCTOXYNOL-9; PHOSPHORIC ACID; SODIUM HYDROXIDE; WATER

Drug Facts

Active ingredient

13% Povidone-Iodine w/w (minimum available Iodine 1%).....................

Purpose

Surgical Hand Scrub

Use

preoperative cleaning of healthcare personnel arms and hands. Significantly reduces the number of micro-organisms on the hands and forearms prior to surgery.

Warnings

For external use only.

Do not use if redness or irritation occurs.

When using this product avoid contact with eyes.

Stop use and ask a doctor if severe adverse reactions occur.

Keep out of reach of children. If swallowed or gets in eyes, get medical help or contact a Poison Control Center immediately.

Directions

- Clean under nails with nail pick
- Wet hands and forearms
- Scrub thoroughly for 3 minutes paying particular attention to the nails, cuticles and interdigital spaces
- Rinse thoroughly
- Repeat scrub for 3 more minutes
- Rinse thoroughly

Other information

- avoid excessive heat 40°C (104°F)
- discard after single use.

Inactive ingredients

ammonium nonoxynol sulfate, disodium phosphate, hydrogen peroxide,

octoxynol, phosphoric acid, sodium hydroxide, USP water.

Questions?

1-800-453-4538 Monday to Friday, 8 a.m. to 5 p.m. MST

Principal Display Panel - BD E-Z Scrub 205 Carton Label

BD

BD E-Z Scrub™ 205

Surgical Scrub Brush/Sponge
and Nail Cleaner
With Povidone-Iodine

Povidone
Iodine

(minimum available Iodine 1%)

CONTAINS:

30

NOTE: SEE BACK PANEL
FOR EASY INSTRUCTIONS

Remove to check level of contents.

Reorder When Brushes Reach This Level.

0130382903720539

REF 372053

NDC 17271-205-03

REMOVE FOR CONVENIENT DISPENSING OF PRODUCT

SEE REVERSE SIDE FOR EASY MOUNTING INSTRUCTIONS